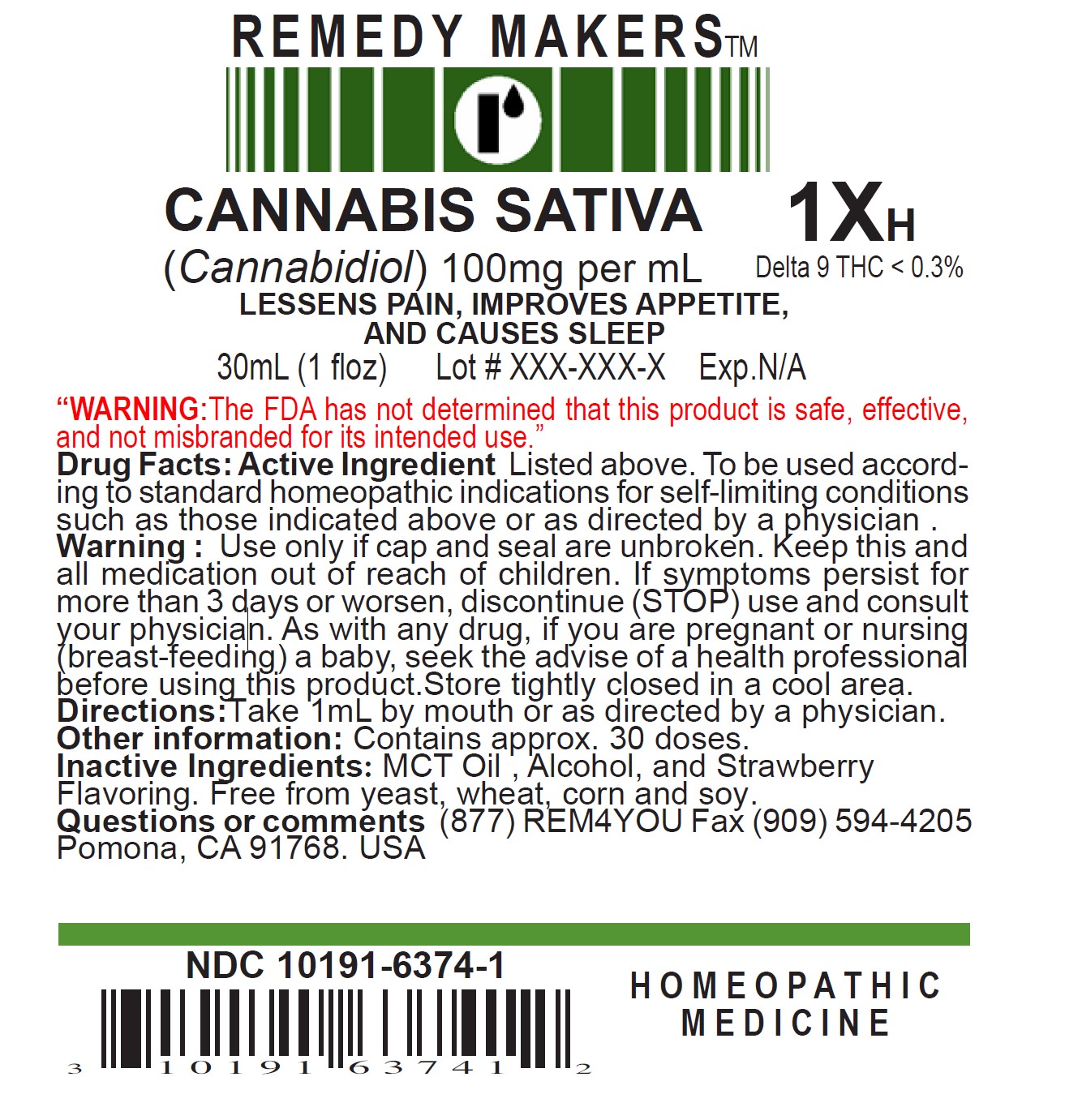 DRUG LABEL: Cannabis Sativa
NDC: 10191-6374 | Form: LIQUID
Manufacturer: Remedy Makers
Category: homeopathic | Type: HUMAN OTC DRUG LABEL
Date: 20230322

ACTIVE INGREDIENTS: CANNABIS SATIVA FLOWERING TOP 1 [hp_X]/30 mL
INACTIVE INGREDIENTS: ALCOHOL; MEDIUM-CHAIN TRIGLYCERIDES

ACTIVE INGREDIENT

CANNABIS SATIVA 1X

(Cannabidiol) 100mg per mL Delta 9 THC < 0.3%

PURPOSE

LESSENS PAIN, IMPROVES APPETITE, AND CAUSES SLEEP

WARNING:

"The FDA has not determined that this product is safe, effective and not misbranded for its intended use."

INDICATIONS AND USAGE

To be used according to standard homeopathic indications for self-limiting conditions such as those indicated above or as directed by a physician.

KEEP OUT OF REACH OF CHILDREN

Keep this and all medication out of reach of children.

Warning:

Use only if cap and seal are unbroken. If symptoms persist for more than 3 days or worsen, discontinue (STOP) use and consult your physician. As with any drug, if you are pregnant or nursing (breast-feeding) a baby, seek the advise of a health professional before using this product. Store tightly closed in a cool area.

Directions:

Take 1mL by mouth or as directed by a physician.

Other information:

Contains approx. 30 doses.

Inactive Ingredients:

MCT Oil, Alcohol, and Strawberry Flavoring. Free from yeast, wheat, corn, and soy.

Questions or comments

(877) REM4YOU Fax (909) 594-4205 Pomona, CA 91768. USA